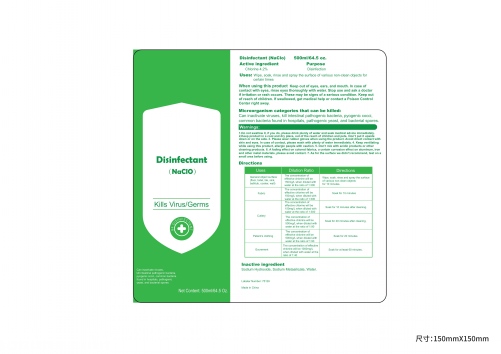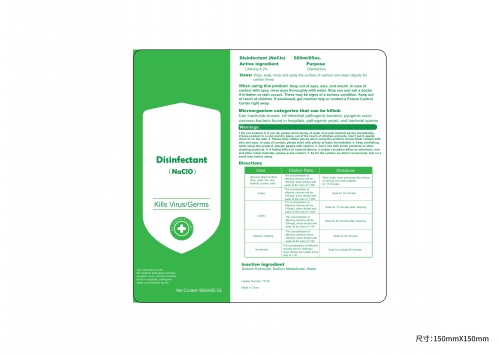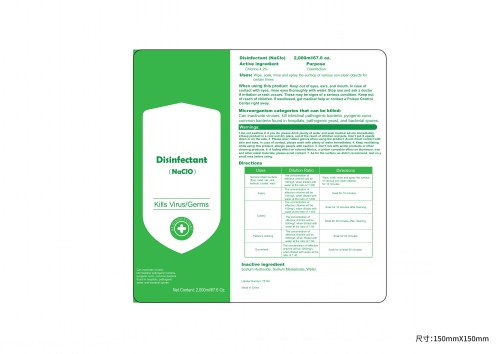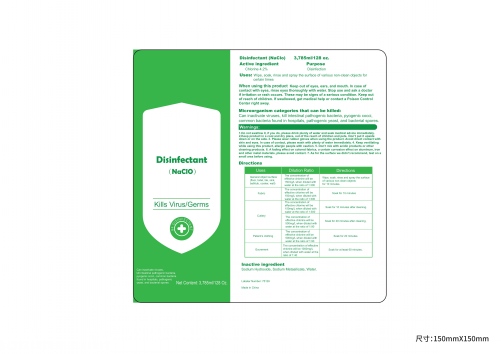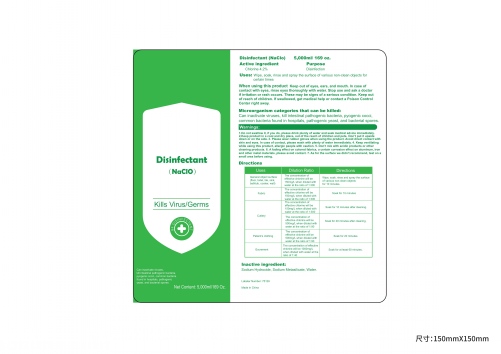 DRUG LABEL: Disinfectant(NaClO)
NDC: 75129-004 | Form: LIQUID
Manufacturer: Shanghai Rayshine ENVI-TECH Developing CO., Ltd.
Category: otc | Type: HUMAN OTC DRUG LABEL
Date: 20200418

ACTIVE INGREDIENTS: CHLORINE 4.2 g/100 mL
INACTIVE INGREDIENTS: WATER; SODIUM METASILICATE; SODIUM HYDROXIDE

Disinfectant(NaClO)

Active ingredient

Chlorine 4.2%

Purpose

Disinfection

Uses

Wipe,soak,rinse and spray the surface of various non-clean objects for certain times.

Warnings

1.Do not swallow it, if you do, please drink plenty of water and seek medical advice immediately.
2.Keep product in a cool and dry place, out of the reach of children and pets. Don’t put it upside down or on the side.

3. Please wear rubber gloves when using the product. Avoid direct contact with skin and eyes. In case of contact, please wash with plenty of water immediately.

4. Keep ventilating while using this product, allergic people with caution.

5. Don’t mix with acidic products or other cleaning products.

6. A fading effect on colored fabrics, a certain corrosion effect on aluminum, iron and other metal materials, please avoid contact.

7. As for the surface we didn’t recommend, test on a small area before using.

When using this product

Keep out of eyes, ears, and mouth. In case of contact with eyes, rinse eyes thoroughly with water. Stop use and ask a doctor
if irritation or rash occurs. These may be signs of a serious condition. Keep out of reach of children. If swallowed, get medical

help or contact a Poison Control Center right away.

Directions

Uses Dilution Ratio Directions

General object surface The concentration of Wipe, soak, rinse and spray the surface

(floor, toilet, tile, sink, effective chlorine will be of various non-clean objects

bathtub, cooker, wall) 150mg/L when diluted with for 10 minutes.

water at the ratio of 1:300

The concentration of

Fabric effective chlorine will be
150mg/L when diluted with Soak for 10 minutes
water at the ratio of 1:300

Cutlery The concentration of Soak for 10 minutes after cleaning.

effective chlorine will be
150mg/L when diluted with
water at the ratio of 1:300
The concentration of
effective chlorine will be Soak for 20 minutes after cleaning.

500mg/L when diluted with
water at the ratio of 1:90

Patient’s clothing The concentration of
effective chlorine will be Soak for 20 minutes.

500mg/L when diluted with
water at the ratio of 1:90

Excrement The concentration of effective
chlorine will be 1000mg/L Soak for at least 60 minutes.

when diluted with water at the
ratio of 1:40

Inactive ingredient

Sodium Hydroxide,Sodium Metasilicate,Water.